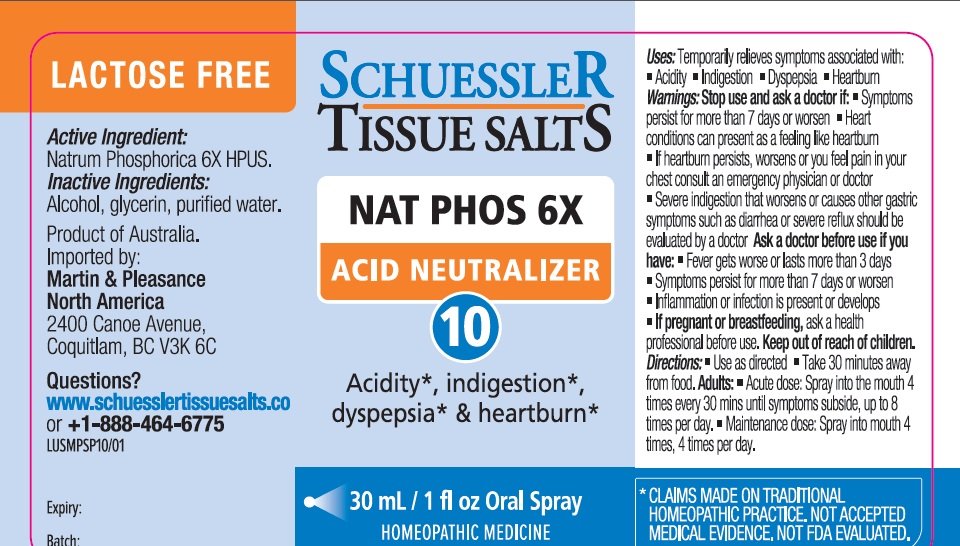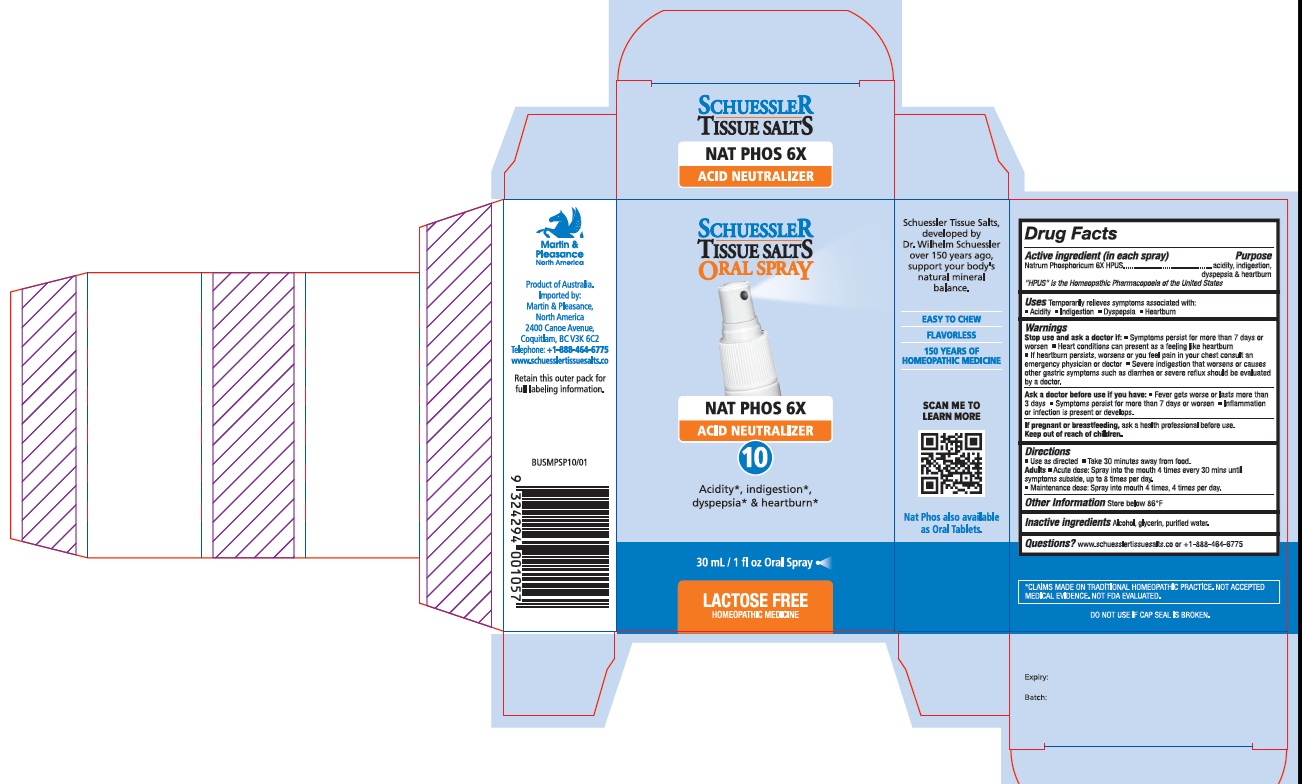 DRUG LABEL: Schuessler Tissue Salts Nat Phos Acid Neutralizer 10
NDC: 84999-010 | Form: SPRAY
Manufacturer: Martin & Pleasance Pty Ltd
Category: homeopathic | Type: HUMAN OTC DRUG LABEL
Date: 20250707

ACTIVE INGREDIENTS: SODIUM PHOSPHATE, DIBASIC, ANHYDROUS 6 [hp_X]/30 mL
INACTIVE INGREDIENTS: ALCOHOL; GLYCERIN; WATER

Active ingredient (in each spray) Purpose

Natrum Phosphoricum 6X HPUS acidity, indigestion, dyspepsia & heartburn

“HPUS” is the Homeopathic Pharmacopoeia of the United States

Uses

Temporarily relieves symptoms associated with:

• Acidity

• Indigestion

• Dyspepsia

• Heartburn

Warnings

Stop use and ask a doctor If:

- Symptoms persist for more than 7 days or worsen
- Heart conditions can present as a feeling like heartburn
- If heartburn persists, worsens or you feel pain in your chest consult an emergency physician or doctor
- Severe indigestion that worsens or causes other gastric symptoms such as diarrhea or severe reflux should be evaluated by a doctor.

Ask a doctor before use if you have:

- Fever gets worse or lasts more than 3 days
- Symptoms persist for more than 7 days or worsen
- Inflammation or infection is present or develops.

If pregnant or breastfeeding, ask a health professional before use. Keep out of reach of children.

Directions

- Use as directed
- Take 30 minutes away from food.

Adults

- Acute dose: Spray into the mouth 4 times every 30 mins until symptoms subside, up to 8 times per day.
- Maintenance dose: Spray into mouth 4 times, 4 times per day.

Other Information

Store below 86°F

Inactive Ingredients

Alcohol, Glycerin, Purified Water

Questions?www.schuesslertissuesalts.co or + 1-888-464-6775